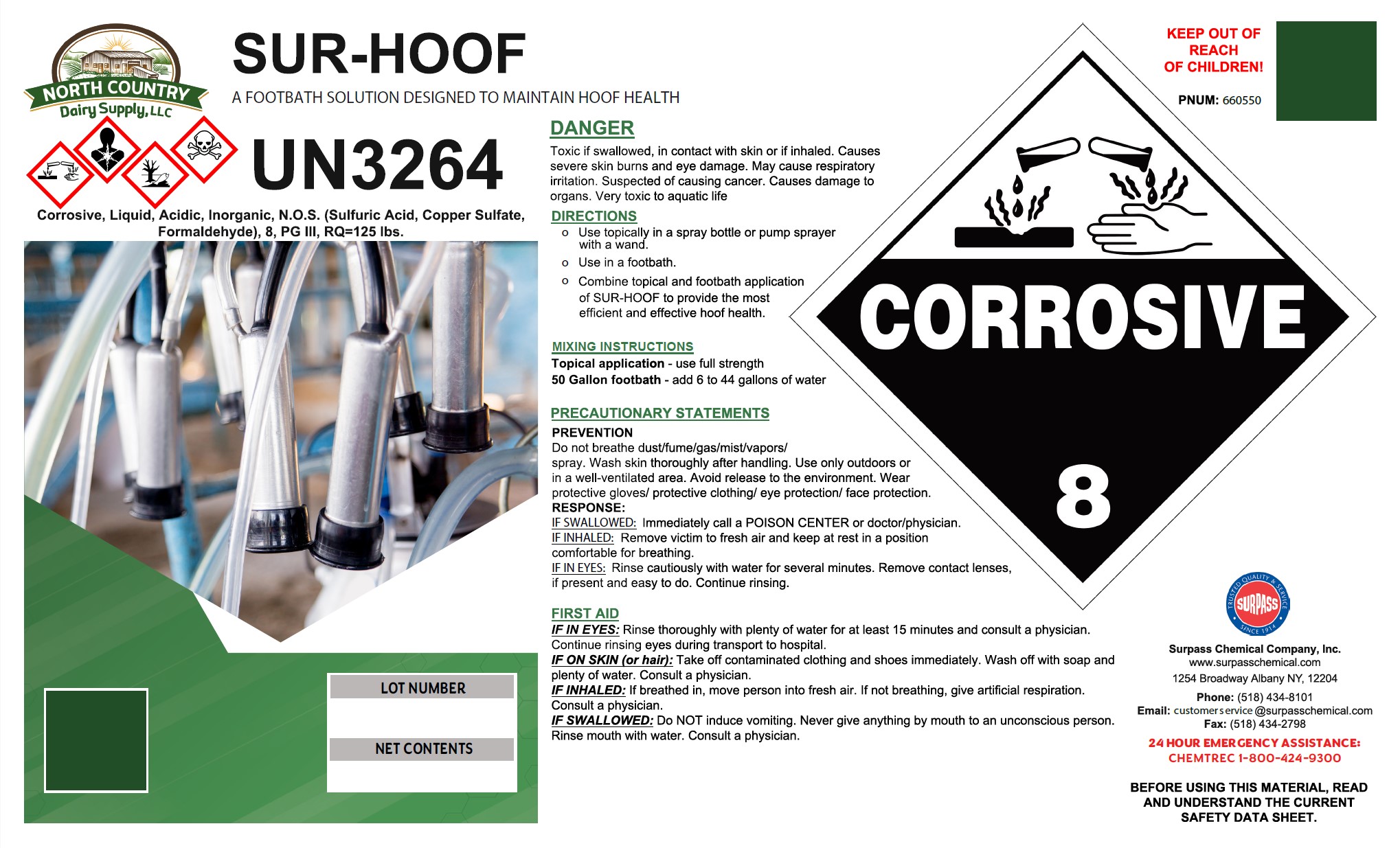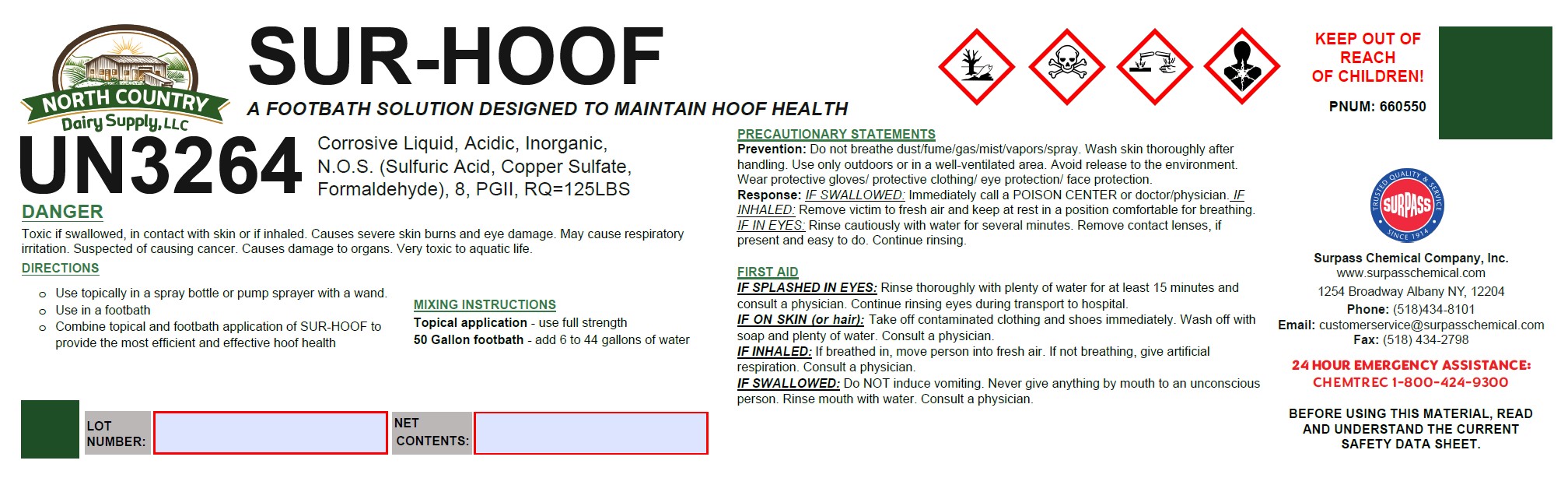 DRUG LABEL: Sur-Hoof
NDC: 86067-0108 | Form: SOLUTION
Manufacturer: Surpass Chemical. Company, Inc.
Category: animal | Type: OTC ANIMAL DRUG LABEL
Date: 20240510

ACTIVE INGREDIENTS: FORMALDEHYDE 0.1667 kg/1 kg
INACTIVE INGREDIENTS: water 0.7325 kg/1 kg; SULFURIC ACID 0.0103 kg/1 kg; ANHYDROUS CITRIC ACID 0.0082 kg/1 kg; BASIC COPPER SULFATE 0.0823 kg/1 kg

SUR-HOOF

DESCRIPTION

SUR-HOOF

A footbath solution designed to maintain hoof health.

DIRECTIONS

- Use topically in a spray bottle or pump sprayer with a wand
- Use in a footbath
- Combine topical and footbath application of SUR-HOOF to provide the most efficient and effective hoof health

MIXING INSTRUCTIONS

Topical application – use full strength

50 gallon footbath – Add 6 gallons to 44 gallons of water

PRECAUTIONS

PRECAUTIONARY STATEMENTS

PREVENTION
Do not breathe dust/fume/gas/mist/vapors/spray. Wash skin thoroughly after handling. Use only outdoors or in a well-ventilated area. Avoid release to the environment. Wear protective gloves/ protective clothing/ eye protection/ face protection.

RESPONSE
IF SWALLOWED: Immediately call a POISON CENTER or doctor/physician

IF INHALED: Remove victim to fresh air and keep at rest in a position comfortable for breathing.

IF IN EYES: Rinse cautiously with water for several minutes. Remove contact lenses, if present and easy to do. Continue rinsing.

OTHER SAFETY INFORMATION

FIRST AID

IF IN EYES: Rinse thoroughly with plenty of water for at least 15 minutes and consult a physician. Continue rinsing eyes during transport to hospital.

IF ON SKIN (or hair): Take off contaminated clothing and shoes immediately. Wash off with soap and plenty of water. Consult a physician.

IF INHALED:If breathed in, move person to fresh air. If not breathing, give artificial respiration. Consult a physician.

IF SWALLOWED:Do NOT induce vomiting. Never give anything by mouth to an unconcious person. Rinse mouth with water. Consult a physician.

KEEP OUT OF

REACH

OF CHILDREN!

Surpass Chemical Company, Inc.

www.surpasschemical.com

1254 Broadway Albany NY 12204

Phone: (518) 434-8101

Email: customerservice@surpasschemical.com

Fax: (518) 434-2798

24 HOUR EMERGENCY ASSISTANCE: CHEMTREC 1-800-424-9300

BEFORE USING THIS MATERIAL, READ AND UNDERSTAND THE CURRENT SAFETY DATA SHEET.